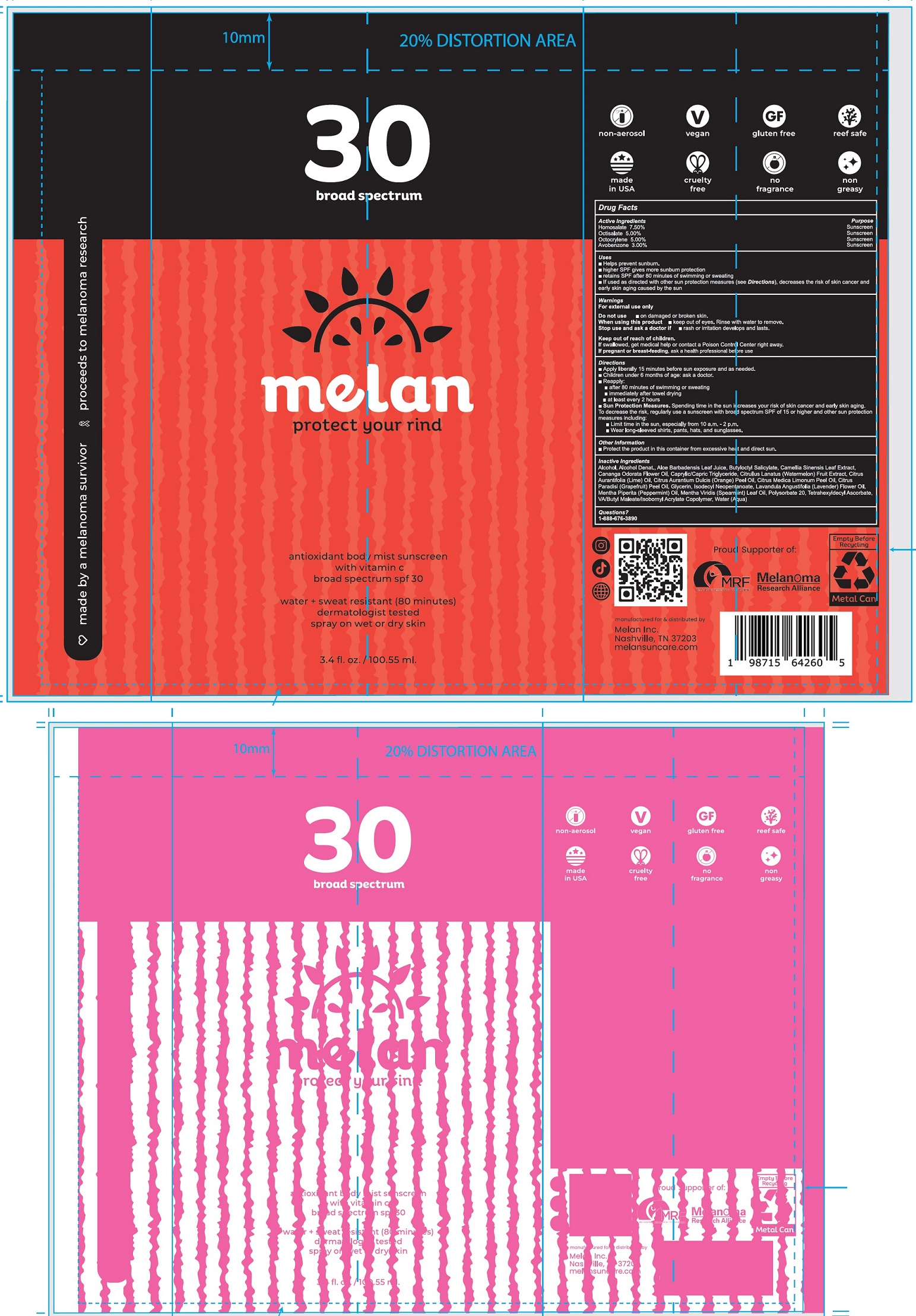 DRUG LABEL: Melan Antioxidant Body Mist Sunscreen SPF 30
NDC: 84294-610 | Form: LIQUID
Manufacturer: MELAN INC.
Category: otc | Type: HUMAN OTC DRUG LABEL
Date: 20250520

ACTIVE INGREDIENTS: HOMOSALATE 75 mg/1 mL; OCTISALATE 50 mg/1 mL; OCTOCRYLENE 50 mg/1 mL; AVOBENZONE 30 mg/1 mL
INACTIVE INGREDIENTS: ALCOHOL; ALOE VERA LEAF JUICE; BUTYLOCTYL SALICYLATE; GREEN TEA LEAF; YLANG-YLANG OIL; MEDIUM-CHAIN TRIGLYCERIDES; WATERMELON; LIME OIL, COLD PRESSED; ORANGE OIL, COLD PRESSED; GRAPEFRUIT OIL; GLYCERIN; ISODECYL NEOPENTANOATE; PEPPERMINT OIL; SPEARMINT OIL; POLYSORBATE 20; TETRAHEXYLDECYL ASCORBATE; WATER

Melan Antioxidant Body Mist Sunscreen SPF 30

Active Ingredients

Homosalate 7.50%
Octisalate 5.00%
Octocrylene 5.00%
Avobenzene 3.00%

Purpose

Sunscreen

Uses

- Helps prevent sunburn.
- higher SPF gives more sunburn protection
- retains SPF after 80 minutes of swimming or sweating
- If used as directed with other sun protection measures (see Directions), decreases the risk of skin cancer and early skin aging caused by the sun

Warnings

For external use only

Do not use

- on damaged or broken skin.

When using this product

- keep out of eyes. Rinse with water to remove.

Stop use and ask a doctor if

- rash or irritation develops and lasts.

Keep out of reach of children.

If swallowed, get medical help or contact a Poison Control Center right away.

If pregnant or breast-feeding,

ask a health professional before use

Directions

- Apply liberally 15 minutes before sun exposure and as needed.
- Children under 6 months of age: ask a doctor.
- Reapply:
- after 80 minutes of swimming or sweating
- immediately after towel drying
- at least every 2 hours
- Sun Protection Measures:Spending time in the sun increases your risk of skin cancer and early skin aging. To decrease this risk, regularly use a sunscreen with broad spectrum SPF of 15 or higher and other sun protection measures including:
- Limit time in the sun, especially from 10 a.m.- 2 p.m.
- Wear long-sleeved shirts, pants, hats, and sunglasses.

Other Information

- Protect the product in this container from excessive heat and direct sun.

Inactive Ingredients

Alcohol, Alcohol Denat., Aloe Barbadensis Leaf Juice, Butyloctyl Salicylate, Camellia Sinensis Leaf Extract, Cananga Odorata Flower Oil, Caprylic/Capric Triglyceride, Citrullus Lanatus (Watermelon) Fruit Extract, Citrus Aurantifolia (Lime) Oil, Citrus Aurantium Dulcis (Orange) Peel Oil, Citrus Medica Limonum Peel Oil, Citrus Paradisi (Grapefruit) Peel Oil, Glycerin, Isodecyl Neopentanoate, Lavendula Angustifolia (Lavander) Flower Oil, Mentha Piperita (Peppermint) Oil, Mentha Viridis (Spearmint) Leaf Oil, Polysorbate 20, Tetrahexyldecyl Ascorbate, VA/Butyl Maleate/Isobornyl Acrylate Copolymer, Water (Aqua)

Questions?

1-888-676-3890